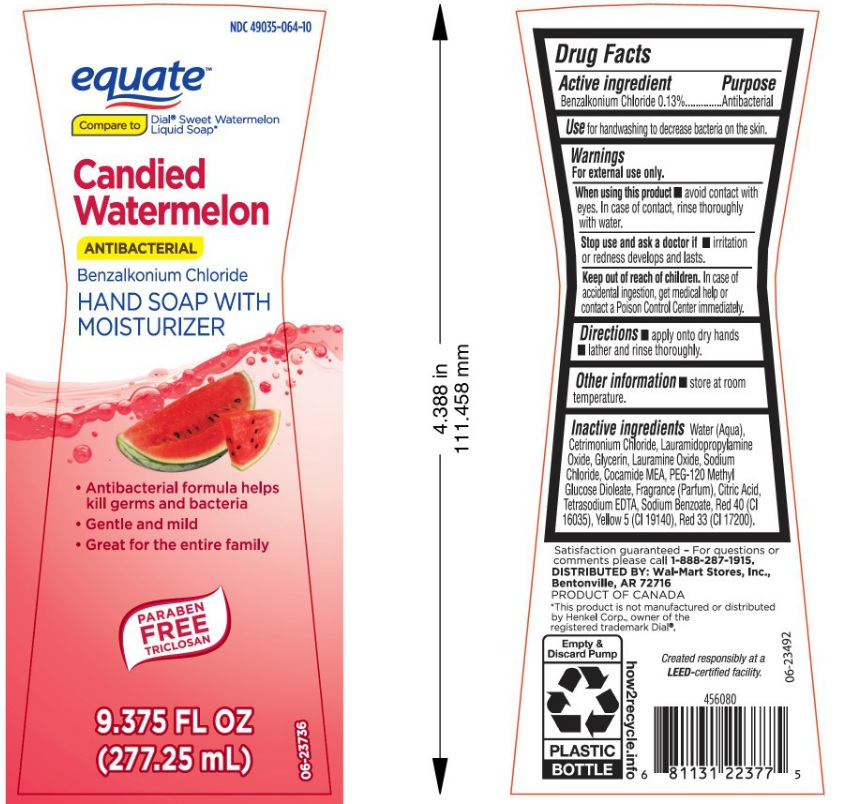 DRUG LABEL: Equate Candied Watermelon Antibacterial Hand
NDC: 49035-064 | Form: SOAP
Manufacturer: Wal-Mart Stores Inc
Category: otc | Type: HUMAN OTC DRUG LABEL
Date: 20180412

ACTIVE INGREDIENTS: BENZALKONIUM CHLORIDE 1.3 mg/1 mL
INACTIVE INGREDIENTS: WATER; CETRIMONIUM CHLORIDE; LAURAMIDOPROPYLAMINE OXIDE; GLYCERIN; LAURAMINE OXIDE; SODIUM CHLORIDE; COCO MONOETHANOLAMIDE; PEG-120 METHYL GLUCOSE DIOLEATE; CITRIC ACID MONOHYDRATE; EDETATE SODIUM; SODIUM BENZOATE; FD&C RED NO. 40; FD&C YELLOW NO. 5; D&C RED NO. 33

Drug Facts

Active ingredient

Benzalkonium Chloride 0.13%

Purpose

Antibacterial

Use

for handwashing to decrease bacteria on the skin.

Warnings

For external use only.

When using this product

- avoid contact with eyes. In case of contact, rinse thoroughly with water.

Stop use and ask a doctor if

- irritation or redness develops and lasts.

Keep out of reach of children.

In case of accidental ingestion, gem medical help or contact a Poison Control Center immediately.

Directions

- apply onto dry hands.
- lather and rinse thoroughly.

Other information

- store at room temperature.

Inactive ingredients

Water (Aqua), Cetrimonium Chloride, Lauramidopropylamine Oxide, Glycerin, Lauramine Oxide, Sodium Chloride, Cocamide MEA, PEG-120 Methyl Glucose Dioleate, Fragrance (Parfum), Citric Acid, Tetrasodium EDTA, Sodium Benzoate, Red 40 (CI 16035), Yellow 5 (CI 19140), Red 33 (CI 17200).